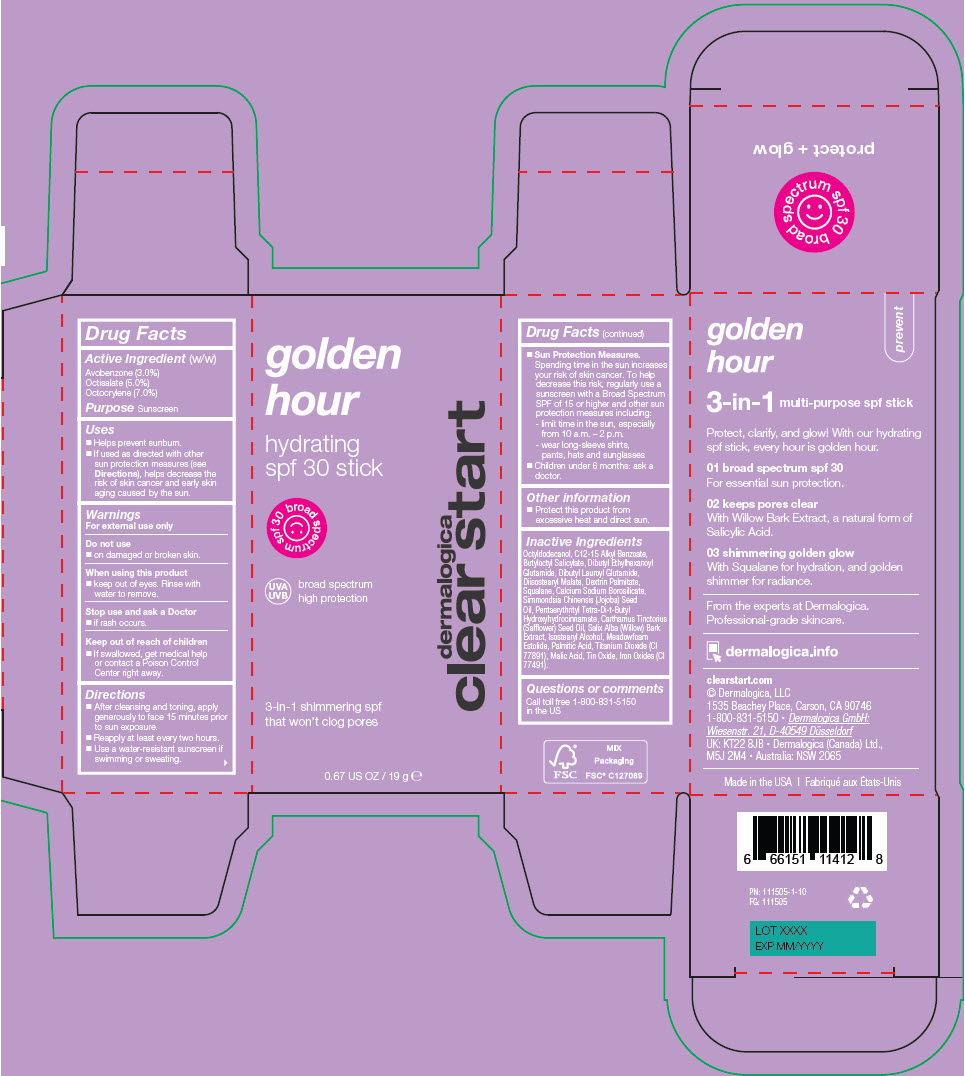 DRUG LABEL: GOLDEN HOUR HYDRATING SPF 30
NDC: 68479-420 | Form: STICK
Manufacturer: Dermalogica, LLC.
Category: otc | Type: HUMAN OTC DRUG LABEL
Date: 20250304

ACTIVE INGREDIENTS: Octocrylene 7 mg/0.1 g; Octisalate 5 mg/0.1 g; Avobenzone 3 mg/0.1 g
INACTIVE INGREDIENTS: Octyldodecanol; ALKYL (C12-15) BENZOATE; Butyloctyl Salicylate; Dibutyl Ethylhexanoyl Glutamide; Dibutyl Lauroyl Glutamide; Diisostearyl Malate; DEXTRIN PALMITATE (CORN; 20000 MW); Squalane; Calcium Sodium Borosilicate; JOJOBA OIL; Meadowfoam Estolide; PENTAERYTHRITOL TETRAKIS(3-(3,5-DI-TERT-BUTYL-4-HYDROXYPHENYL)PROPIONATE); Isostearyl Alcohol; TITANIUM DIOXIDE; SAFFLOWER OIL; Palmitic Acid; Malic Acid; STANNIC OXIDE; FERRIC OXIDE RED; SALIX ALBA BARK

GOLDEN HOUR HYDRATING SPF 30 STICK

Drug Facts

Active Ingredient (w/w)

Avobenzone (3.0%)
Octisalate (5.0%)
Octocrylene (7.0%)

Purpose

Sunscreen

Uses

- Helps prevent sunburn.
- If used as directed with other sun protection measures (see Directions), helps decrease the risk of skin cancer and early skin aging caused by the sun.

Warnings

For external use only

Do not use

- on damaged or broken skin.

When using this product

- keep out of eyes. Rinse with water to remove.

Stop use and ask a Doctor

- if rash occurs.

Keep out of reach of children

- If swallowed, get medical help or contact a Poison Control Center right away.

Directions

- After cleansing and toning, apply generously to face 15 minutes prior to sun exposure.
- Reapply at least every two hours.
- Use a water-resistant sunscreen if swimming or sweating.
- Sun Protection Measures.
  Spending time in the sun increases your risk of skin cancer. To help decrease this risk, regularly use a sunscreen with a Broad Spectrum SPF of 15 or higher and other sun protection measures including:
  - limit time in the sun, especially from 10 a.m. – 2 p.m.
  - wear long-sleeve shirts, pants, hats and sunglasses
- Children under 6 months: ask a doctor.

Other information

- Protect this product from excessive heat and direct sun.

Inactive Ingredients

Octyldodecanol, C12-15 Alkyl Benzoate, Butyloctyl Salicylate, Dibutyl Ethylhexanoyl Glutamide, Dibutyl Lauroyl Glutamide, Diisostearyl Malate, Dextrin Palmitate, Squalane, Calcium Sodium Borosilicate, Simmondsia Chinensis (Jojoba) Seed Oil, Pentaerythrityl Tetra-Di-t-Butyl Hydroxyhydrocinnamate, Carthamus Tinctorius (Safflower) Seed Oil, Salix Alba (Willow) Bark Extract, Isostearyl Alcohol, Meadowfoam Estolide, Palmitic Acid, Titanium Dioxide (CI 77891), Malic Acid, Tin Oxide, Iron Oxides (CI 77491).

Questions or comments

Call toll free 1-800-831-5150 in the US

PRINCIPAL DISPLAY PANEL - 19 g Bottle Carton

golden
hour

hydrating
spf 30 stick

spf 30 broad spectrum

UVA
UVB

broad spectrum
high protection

3-in-1 shimmering spf
that won't clog pores

dermalogica
clear start

0.67 US OZ / 19 g ℮